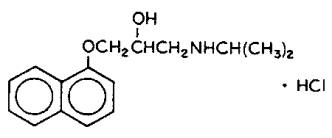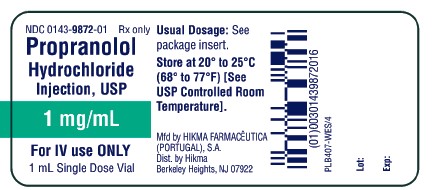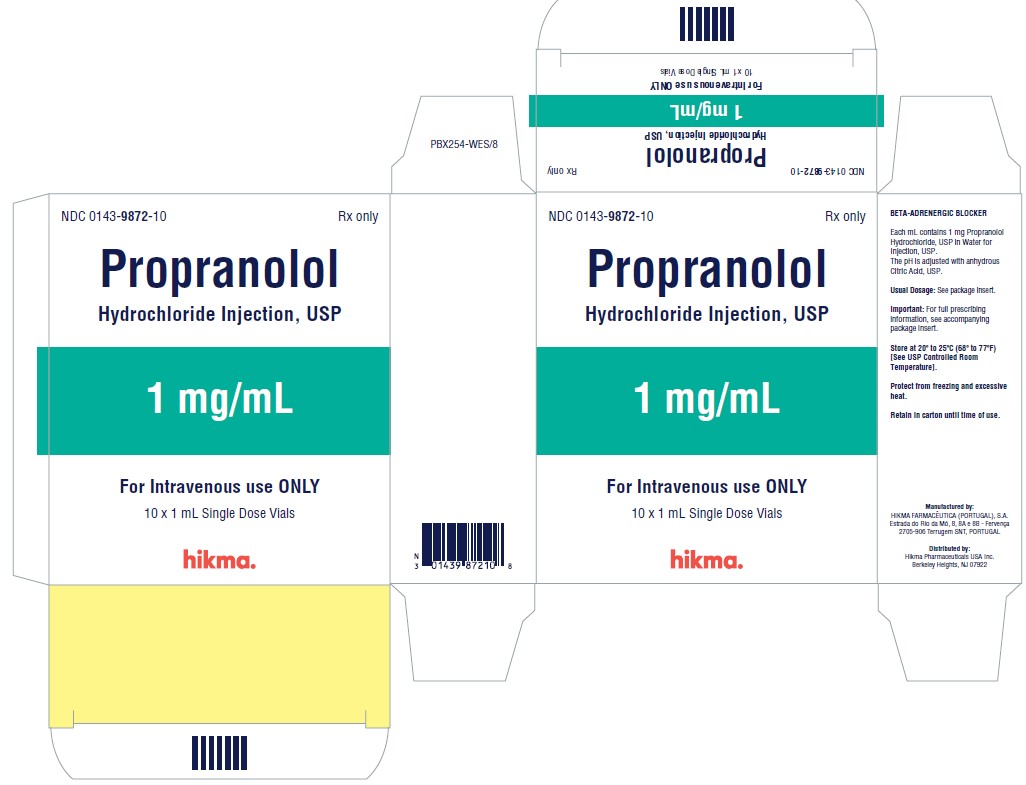 DRUG LABEL: Propranolol Hydrochloride
NDC: 0143-9872 | Form: INJECTION
Manufacturer: Hikma Pharmaceuticals USA Inc.
Category: prescription | Type: HUMAN PRESCRIPTION DRUG LABEL
Date: 20260112

ACTIVE INGREDIENTS: PROPRANOLOL HYDROCHLORIDE 1 mg/1 mL
INACTIVE INGREDIENTS: WATER; ANHYDROUS CITRIC ACID

PROPRANOLOL HYDROCHLORIDE INJECTION, USP

Rx Only

DESCRIPTION

Propranolol Hydrochloride, USP is a synthetic beta-adrenergic receptor blocking agent chemically described as (+)-1-(isopropylamino)-3-(1-naphthyloxy)-2-propanol hydrochloride. Its structural formula is:

C16H21NO2•HCl

Propranolol Hydrochloride, USP is a stable, white, crystalline solid which is readily soluble in water and ethanol. Its molecular weight is 295.80.

Propranolol Hydrochloride Injection, USP is available as a sterile injectable solution for intravenous administration. Each mL contains 1 mg of Propranolol Hydrochloride, USP in Water for Injection, USP. The pH is adjusted with anhydrous Citric Acid, USP.

CLINICAL PHARMACOLOGY

General

Propranolol is a nonselective beta-adrenergic receptor blocking agent possessing no other autonomic nervous system activity. It specifically competes with beta-adrenergic receptor stimulating agents for available receptor sites. When access to beta‑receptor sites is blocked by propranolol, chronotropic, inotropic, and vasodilator responses to beta-adrenergic stimulation are decreased proportionately. At doses greater than required for beta blockade, propranolol also exerts a quinidine-like or anesthetic-like membrane action, which affects the cardiac action potential. The significance of the membrane action in the treatment of arrhythmias is uncertain.

Mechanism of Action

The effects of propranolol are due to selective blockade of beta-adrenergic receptors, leaving alpha-adrenergic responses intact. There are two well-characterized subtypes of beta receptors (beta1 and beta2); propranolol interacts with both subtypes equally. Beta1-adrenergic receptors are found primarily in the heart. Blockade of cardiac beta1-adrenergic receptors leads to a decrease in the activity of both normal and ectopic pacemaker cells and a decrease in A-V nodal conduction velocity. All of these actions can contribute to antiarrhythmic activity and control of ventricular rate during arrhythmias. Blockade of cardiac beta1‑adrenergic receptors also decreases the myocardial force of contraction and may provoke cardiac decompensation in patients with minimal cardiac reserve.

Beta2-adrenergic receptors are found predominantly in smooth muscle–vascular, bronchial, gastrointestinal and genitourinary. Blockade of these receptors results in constriction. Clinically, propranolol may exacerbate respiratory symptoms in patients with obstructive pulmonary diseases such as asthma and emphysema (see CONTRAINDICATIONS and WARNINGS).

Propranolol’s beta blocking effects are attributable to its S(-) enantiomer.

Pharmacokinetics and Drug Metabolism

Distribution

Propranolol has a distribution half-life (T½ alpha) of 5-10 minutes and a volume of distribution of about 4 to 5 L/kg. Approximately 90% of circulating propranolol is bound to plasma proteins. The binding is enantiomer-selective. The S-isomer is preferentially bound to alpha1 glycoprotein and the R-isomer is preferentially bound to albumin.

Metabolism and Elimination

The elimination half-life (T½ beta) is between 2 and 5.5 hours. Propranolol is extensively metabolized with most metabolites appearing in the urine. The major metabolites include propranolol glucuronide, naphthyloxylactic acid, and glucuronic acid and sulfate conjugates of 4-hydroxy propranolol. Following single-dose intravenous administration, side-chain oxidative products account for approximately 40% of the metabolites, direct conjugation products account for approximately 45-50% of metabolites, and ring oxidative products account for approximately 10-15% of metabolites. Of these, only the primary ring oxidative product (4-hydroxypropranolol) possesses beta-adrenergic receptor blocking activity.

In vitro studies have indicated that the aromatic hydroxylation of propranolol is catalyzed mainly by polymorphic CYP2D6. Side‑chain oxidation is mediated mainly by CYP1A2 and to some extent by CYP2D6. 4-hydroxy propranolol is a weak inhibitor of CYP2D6.

Pharmacodynamics

As propranolol concentration increases, so does its beta-blocking effect, as evidenced by a reduction in exercise-induced tachycardia (n = 6 normal volunteers).

Special Populations

Pediatric

The pharmacokinetics of propranolol have not been investigated in patients under 18 years of age. Propranolol injection is not recommended for treatment of cardiac arrhythmias in pediatric patients.

Geriatric

Elevated propranolol plasma concentrations, a longer mean elimination half-life (254 vs. 152 minutes), and decreased systemic clearance (8 vs. 13 mL/kg/min) have been observed in elderly subjects when compared to young subjects. However, the apparent volume of distribution seems to be similar in elderly and young subjects. These findings suggest that dose adjustment of propranolol injection may be required for elderly patients (see PRECAUTIONS).

Gender

Intravenously administered propranolol was evaluated in 5 women and 6 men. When adjusted for weight, there were no gender-related differences in elimination half-life, volume of distribution, protein binding, or systemic clearance.

Obesity

In a study of intravenously administered propranolol, obese subjects had a higher AUC (161 versus 109 hr·mcg/L) and lower total clearance than did non-obese subjects. Propranolol plasma protein binding was similar in both groups.

Renal Insufficiency

The pharmacokinetics of propranolol and its metabolites were evaluated in 15 subjects with varying degrees of renal function after propranolol administration via the intravenous and oral routes. When compared with normal subjects, an increase in fecal excretion of propranolol conjugates was observed in patients with increased renal impairment. Propranolol was also evaluated in 5 patients with chronic renal failure, 6 patients on regular dialysis, and 5 healthy subjects, following a single oral dose of 40 mg of propranolol. The peak plasma concentrations (Cmax) of propranolol in the chronic renal failure group were 2- to 3-fold higher (161 ng/mL) than those observed in the dialysis patients (47 ng/mL) and in the healthy subjects (26 ng/mL). Propranolol plasma clearance was also reduced in the patients with chronic renal failure.

Chronic renal failure has been associated with a decrease in drug metabolism via downregulation of hepatic cytochrome P-450 activity.

Hepatic Insufficiency

Propranolol is extensively metabolized by the liver. In a study conducted in 6 normal subjects and 20 patients with chronic liver disease, including hepatic cirrhosis, 40 mg of R-propranolol was administered intravenously. Compared to normal subjects, patients with chronic liver disease had decreased clearance of propranolol, increased volume of distribution, decreased protein-binding, and considerable variation in half-life. Caution should be exercised when propranolol is used in this population. Consideration should be given to lowering the dose of intravenous propranolol in patients with hepatic insufficiency (see PRECAUTIONS).

Thyroid Dysfunction

No pharmacokinetic changes were observed in hyperthyroid or hypothyroid patients when compared to their corresponding euthyroid state. Dosage adjustment does not seem necessary in either patient population based on pharmacokinetic findings.

Drug Interactions

Interactions with Substrates, Inhibitors or Inducers of Cytochrome P-450 Enzymes

Because propranolol’s metabolism involves multiple pathways in the cytochrome P-450 system (CYP2D6, 1A2, 2C19), administration of propranolol with drugs that are metabolized by, or affect the activity (induction or inhibition) of one or more of these pathways may lead to clinically relevant drug interactions (see PRECAUTIONS, Drug Interactions).

Substrates or Inhibitors of CYP2D6

Blood levels of propranolol may be increased by administration of propranolol with substrates or inhibitors of CYP2D6, such as amiodarone, cimetidine, delavirdine, fluoxetine, paroxetine, quinidine, and ritonavir. No interactions were observed with either ranitidine or lansoprazole.

Substrates or Inhibitors of CYP1A2

Blood levels of propranolol may be increased by administration of propranolol with substrates or inhibitors of CYP1A2, such as imipramine, cimetidine, ciprofloxacin, fluvoxamine, isoniazid, ritonavir, theophylline, zileuton, zolmitriptan, and rizatriptan.

Substrates or Inhibitors of CYP2C19

Blood levels of propranolol may be increased by administration of propranolol with substrates or inhibitors of CYP2C19, such as fluconazole, cimetidine, fluoxetine, fluvoxamine, teniposide, and tolbutamide. No interaction was observed with omeprazole.

Inducers of Hepatic Drug Metabolism

Blood levels of propranolol may be decreased by administration of propranolol with inducers such as rifampin and ethanol. Cigarette smoking also induces hepatic metabolism and has been shown to increase up to 100% the clearance of propranolol, resulting in decreased plasma concentrations.

Cardiovascular Drugs

Antiarrhythmics

The AUC of propafenone is increased by more than 200% with co-administration of propranolol.

The metabolism of propranolol is reduced by co-administration of quinidine, leading to a 2- to 3-fold increased blood concentrations and greater beta-blockade.

The metabolism of lidocaine is inhibited by co-administration of propranolol, resulting in a 25% increase in lidocaine concentrations.

Calcium Channel Blockers

The mean Cmax and AUC of propranolol are increased respectively, by 50% and 30% by co-administration of nisoldipine and by 80% and 47%, by co-administration of nicardipine.

The mean values of Cmax and AUC of nifedipine are increased by 64% and 79%, respectively, by co-administration of propranolol.

Propranolol does not affect the pharmacokinetics of verapamil and norverapamil. Verapamil does not affect the pharmacokinetics of propranolol.

Non-Cardiovascular Drugs

Migraine Drugs

Administration of zolmitriptan or rizatriptan with propranolol resulted in increased concentrations of zolmitriptan (AUC increased by 56% and Cmax by 37%) or rizatriptan (the AUC and Cmax were increased by 67% and 75%, respectively).

Theophylline

Co-administration of theophylline with propranolol decreases theophylline clearance by 33% to 52%.

Benzodiazepines

Propranolol can inhibit the metabolism of diazepam, resulting in increased concentrations of diazepam and its metabolites. Diazepam does not alter the pharmacokinetics of propranolol.

The pharmacokinetics of oxazepam, triazolam, lorazepam, and alprazolam are not affected by co-administration of propranolol.

Neuroleptic Drugs

Co-administration of propranolol at doses greater than or equal to 160 mg/day resulted in increased thioridazine plasma concentrations ranging from 50% to 370% and increased thioridazine metabolites concentrations ranging from 33% to 210%.

Co-administration of chlorpromazine with propranolol resulted in increased plasma levels of both drugs (70% increase in propranolol concentrations).

Anti-Ulcer Drugs

Co-administration of propranolol with cimetidine, a non-specific CYP450 inhibitor, increased propranolol concentrations by about 40%. Co‑administration with aluminum hydroxide gel (1200 mg) resulted in a 50% decrease in propranolol concentrations.

Co-administration of metoclopramide with propranolol did not have a significant effect on propranolol’s pharmacokinetics.

Lipid Lowering Drugs

Co-administration of cholesteramine or colestipol with propranolol resulted in up to 50% decrease in propranolol concentrations.

Co-administration of propranolol with lovastatin or pravastatin decreased 20% to 25% the AUC of both, but did not alter their pharmacodynamics. Propranolol did not have an effect on the pharmacokinetics of fluvastatin.

Warfarin

Concomitant administration of propranolol and warfarin has been shown to increase warfarin bioavailability and increase prothrombin time.

CLINICAL STUDIES

In a series of 225 patients with supraventricular (n = 145), ventricular (n = 69), or both (n = 11) arrythmias resistant to digitalis, intravenous propranolol hydrochloride was administered in single doses, averaging 1 to 5 mg. Approximately one-quarter of the patients with supraventricular arrhythmias (generally those with sinus or atrial tachycardia) reverted to normal sinus rhythm. About one-half had symptoms ameliorated either by a decrease in ventricular rate or an attenuation of frequency or severity of paroxysmal attacks.

Approximately one-half of patients with ventricular arrhythmias (generally those with frequent PVCs) reverted to normal sinus rhythm or responded with a reduction in ventricular rate.

Similar findings were seen in a series of 25 Bantu patients with atrial fibrillation (n = 16), sinus tachycardia (n = 5), and multifocal ventricular extrasystoles (n = 9).

In another series, 7 of 8 patients with digitalis-related tachyarrhythmia had ventricular rate decreases after intravenous propranolol. Similarly limited clinical experience has shown that intravenous propranolol will slow the ventricular rate in patients with Wolff-Parkinson-White syndrome or with tachycardia associated with thyrotoxicosis.

Onset of activity is usually within five minutes.

INDICATIONS AND USAGE

Cardiac Arrhythmias

Intravenous administration is usually reserved for life-threatening arrhythmias or those occurring under anesthesia.

1. Supraventricular arrhythmias
Intravenous propranolol is indicated for the short-term treatment of supraventricular tachycardia, including Wolff‑Parkinson‑White syndrome and thyrotoxicosis, to decrease ventricular rate. Use in patients with atrial flutter or atrial fibrillation should be reserved for arrythmias unresponsive to standard therapy or when more prolonged control is required. Reversion to normal sinus rhythm has occasionally been observed, predominantly in patients with sinus or atrial tachycardia.

2. Ventricular tachycardias
With the exception of those induced by catecholamines or digitalis, propranolol is not the drug of first choice. In critical situations when cardioversion techniques or other drugs are not indicated or are not effective, propranolol may be considered. If, after consideration of the risks involved, propranolol is used, it should be given intravenously in low dosage and very slowly, as the failing heart requires some sympathetic drive for maintenance of myocardial tone (see DOSAGE AND ADMINISTRATION). Some patients may respond with complete reversion to normal sinus rhythm, but reduction in ventricular rate is more likely. Ventricular arrhythmias do not respond to propranolol as predictably as do the supraventricular arrhythmias.
Intravenous propranolol is indicated for the treatment of persistent premature ventricular extrasystoles that impair the well‑being of the patient and do not respond to conventional measures.

3. Tachyarrhythmias of digitalis intoxication
Intravenous propranolol is indicated to control ventricular rate in life-threatening digitalis-induced arrhythmias. Severe bradycardia may occur (see OVERDOSAGE).

4. Resistant tachyarrhythmias due to excessive catecholamine action during anesthesia
Intravenous propranolol is indicated to abolish tachyarrhythmias due to excessive catecholamine action during anesthesia when other measures fail. These arrhythmias may arise because of release of endogenous catecholamines or administration of catecholamines. All general inhalation anesthetics produce some degree of myocardial depression. Therefore, when propranolol is used to treat arrhythmias during anesthesia, it should be used with extreme caution, usually with constant monitoring of the ECG and central venous pressure (see WARNINGS).

CONTRAINDICATIONS

Propranolol is contraindicated in 1) cardiogenic shock; 2) sinus bradycardia and greater than first-degree block; 3) bronchial asthma; and 4) in patients with known hypersensitivity to propranolol hydrochloride.

WARNINGS

Cardiac Failure

Sympathetic stimulation may be a vital component supporting circulatory function in patients with congestive heart failure, and its inhibition by beta blockade may precipitate more severe failure. Although beta‑blockers should be avoided in overt congestive heart failure, some have been shown to be highly beneficial when used with close follow-up in patients with a history of failure who are well compensated and are receiving additional therapies, including diuretics as needed. Beta-adrenergic blocking agents do not abolish the inotropic action of digitalis on heart muscle.

Nonallergic Bronchospasm (e.g., Chronic Bronchitis, Emphysema)

In general, patients with bronchospastic lung disease should not receive beta blockers. Propranolol should be administered with caution in this setting since it may block bronchodilation produced by endogenous and exogenous catecholamine stimulation of beta-receptors.

Major Surgery

The necessity or desirability of withdrawal of beta-blocking therapy prior to major surgery is controversial. It should be noted, however, that the impaired ability of the heart to respond to reflex adrenergic stimuli in propranolol-treated patients might augment the risks of general anesthesia and surgical procedures.

Propranolol is a competitive inhibitor of beta-receptor agonists, and its effects can be reversed by administration of such agents, e.g., dobutamine or isoproterenol. However, such patients may be subject to protracted severe hypotension.

Diabetes and Hypoglycemia

Beta-adrenergic blockade may prevent the appearance of certain premonitory signs and symptoms (pulse rate and pressure changes) of acute hypoglycemia, especially in labile insulin-dependent diabetics. In these patients, it may be more difficult to adjust the dosage of insulin.

Propranolol therapy, particularly in infants and children, diabetic or not, has been associated with hypoglycemia especially during fasting, as in preparation for surgery. Hypoglycemia has been reported after prolonged physical exertion and in patients with renal insufficiency.

Thyrotoxicosis

Beta-adrenergic blockade may mask certain clinical signs of hyperthyroidism. Therefore, abrupt withdrawal of propranolol may be followed by an exacerbation of symptoms of hyperthyroidism, including thyroid storm. Propranolol may change thyroid-function tests, increasing T4 and reverse T3, and decreasing T3.

Wolff-Parkinson-White Syndrome

Beta-adrenergic blockade in patients with Wolff-Parkinson-White syndrome and tachycardia has been associated with severe bradycardia requiring treatment with a pacemaker. In one case this resulted after an initial 5 mg dose of intravenous propranolol.

PRECAUTIONS

General

Propranolol should be used with caution in patients with impaired hepatic or renal function. Propranolol is not indicated for the treatment of hypertensive emergencies.

Beta-adrenergic receptor blockade can cause reduction of intraocular pressure. Patients should be told that propranolol might interfere with the glaucoma screening test. Withdrawal may lead to a return of elevated intraocular pressure.

Risk of anaphylactic reaction. While taking beta-blockers, patients with a history of severe anaphylactic reaction to a variety of allergens may be more reactive to repeated challenge, either accidental, diagnostic, or therapeutic. Such patients may be unresponsive to the usual doses of epinephrine used to treat allergic reaction.

Angina Pectoris

There have been reports of exacerbation of angina and, in some cases, myocardial infarction, following abrupt discontinuance of propranolol therapy. Therefore, when discontinuance of propranolol is planned, the dosage should be gradually reduced over at least a few weeks, and the patient should be cautioned against interruption or cessation of therapy without a physician’s advice. If propranolol therapy is interrupted and exacerbation of angina occurs, it is usually advisable to reinstitute propranolol therapy and take other measures appropriate for the management of angina pectoris. Since coronary artery disease may be unrecognized, it may be prudent to follow the above advice in patients considered at risk of having occult atherosclerotic heart disease who are given propranolol for other indications.

Clinical Laboratory Tests

In patients with hypertension, use of propranolol has been associated with elevated levels of serum potassium, serum transaminases and alkaline phosphatase. In severe heart failure, the use of propranolol has been associated with increases in Blood Urea Nitrogen.

Drug Interactions

Caution should be exercised when propranolol is administered with drugs that have an effect on CYP2D6, 1A2, or 2C19 metabolic pathways. Co-administration of such drugs with propranolol may lead to clinically relevant drug interactions and changes in its efficacy and/or toxicity (see CLINICAL PHARMACOLOGY, Drug Interactions).

Cardiovascular Drugs

Antiarrhythmics

Propafenone has negative inotropic and beta-blocking properties that can be additive to those of propranolol.

Quinidine increases the concentration of propranolol and produces a greater degree of clinical beta-blockade and may cause postural hypotension.

Disopyramide is a Type I antiarrhythmic drug with potent negative inotropic and chronotropic effects and has been associated with severe bradycardia, asystole and heart failure when administered with propranolol.

Amiodarone is an antiarrhythmic agent with negative chronotropic properties that may be additive to those seen with propranolol.

The clearance of lidocaine is reduced when administered with propranolol. Lidocaine toxicity has been reported following co-administration with propranolol.

Caution should be exercised when administering propranolol with drugs that slow A-V nodal conduction, e.g., digitalis, lidocaine and calcium channel blockers.

Calcium Channel Blockers

Caution should be exercised when patients receiving a beta-blocker are administered a calcium-channel-blocking drug with negative inotropic and/or chronotropic effects. Both agents may depress myocardial contractility or atrioventricular conduction.

There have been reports of significant bradycardia, heart failure, and cardiovascular collapse with concurrent use of verapamil and beta‑blockers.

Co-administration of propranolol and diltiazem in patients with cardiac disease has been associated with bradycardia, hypotension, high degree heart block, and heart failure.

ACE Inhibitors

When combined with beta-blockers, ACE inhibitors can cause hypotension, particularly in the setting of acute myocardial infarction.

ACE inhibitors have been reported to increase bronchial hyperreactivity when administered with propranolol.

The antihypertensive effects of clonidine may be antagonized by beta-blockers. Propranolol should be administered cautiously to patients withdrawing from clonidine.

Alpha-blockers

Prazosin has been associated with prolongation of first dose hypotension in the presence of beta-blockers.

Postural hypotension has been reported in patients taking both beta-blockers and terazosin or doxazosin.

Reserpine

Patients receiving catecholamine-depleting drugs, such as reserpine, with propranolol should be closely observed for excess reduction of resting sympathetic nervous activity, which may result in hypotension, marked bradycardia, vertigo, syncopal attacks, or orthostatic hypotension. Administration of reserpine with propranolol may also potentiate depression.

Inotropic Agents

Patients on long-term therapy with propranolol may experience uncontrolled hypertension if administered epinephrine as a consequence of unopposed alpha-receptor stimulation. Epinephrine is therefore not indicated in the treatment of propranolol overdose (see OVERDOSAGE).

Isoproterenol and Dobutamine

Propranolol is a competitive inhibitor of beta-receptor agonists, and its effects can be reversed by administration of such agents, e.g., dobutamine or isoproterenol. Also, propranolol may reduce sensitivity to dobutamine stress echocardiography in patients undergoing evaluation for myocardial ischemia.

Non-Cardiovascular Drugs

Non-steroidal anti-inflammatory drugs (NSAIDs) have been reported to blunt the antihypertensive effect of beta-adrenoreceptor blocking agents.

Administration of indomethacin with propranolol may reduce the efficacy of propranolol in reducing blood pressure and heart rate.

Antidepressants

The hypotensive effects of MAO inhibitors or tricyclic antidepressants may be exacerbated when administered with beta-blockers by interfering with the beta blocking activity of propranolol.

Anesthetic Agents

Methoxyflurane and trichloroethylene may depress myocardial contractility when administered with propranolol.

Warfarin

Administration of propranolol with warfarin increases the concentration of warfarin. Therefore, the prothrombin time should be monitored.

Neuroleptic Drugs

Hypotension and cardiac arrest have been reported with the concomitant use of propranolol and haloperidol.

Thyroxine

Thyroxine may result in a lower than expected T3 concentration when used concomitantly with propranolol.

Carcinogenesis, Mutagenesis, Impairment of Fertility

In dietary administration studies in which mice and rats were treated with propranolol hydrochloride for up to 18 months at doses of up to 150 mg/kg/day, there was no evidence of drug-related tumorigenesis. On a body surface area basis, this dose in the mouse and rat is, respectively, about equal to and about twice the maximum recommended human oral daily dose (MRHD) of 640 mg propranolol hydrochloride. In a study in which both male and female rats were exposed to propranolol hydrochloride in their diets at concentrations of up to 0.05% (about 50 mg/kg body weight and less than the MRHD), from 60 days prior to mating and throughout pregnancy and lactation for two generations, there were no effects on fertility. Based on differing results from Ames Tests performed by different laboratories, there is equivocal evidence for a genotoxic effect of propranolol hydrochloride in bacteria (S. typhimurium strain TA 1538).

Pregnancy

In a series of reproductive and developmental toxicology studies, propranolol hydrochloride was given to rats by gavage or in the diet throughout pregnancy and lactation. At doses of 150 mg/kg/day, but not at doses of 80 mg/kg/day (equivalent to the MRHD on a body surface area basis), treatment was associated with embryotoxicity (reduced litter size and increased resorption rates) as well as neonatal toxicity (deaths). Propranolol hydrochloride also was administered (in the feed) to rabbits (throughout pregnancy and lactation) at doses as high as 150 mg/kg/day (about 5 times the maximum recommended human oral daily dose). No evidence of embryo or neonatal toxicity was noted.

There are no adequate and well-controlled studies in pregnant women. Intrauterine growth retardation has been reported for neonates whose mothers received propranolol hydrochloride during pregnancy. Neonates whose mothers received propranolol hydrochloride at parturition have exhibited bradycardia, hypoglycemia, and respiratory depression. Adequate facilities for monitoring such infants at birth should be available. Propranolol should be used during pregnancy only if the potential benefit justifies the potential risk to the fetus.

Nursing Mothers

Propranolol is excreted in human milk. Caution should be exercised when propranolol is administered to a nursing woman.

Pediatric Use

Safety and effectiveness of propranolol in pediatric patients have not been established.

Geriatric Use

Clinical studies of intravenous propranolol did not include sufficient numbers of subjects aged 65 and over to determine whether they respond differently from younger subjects. Elderly subjects have decreased clearance and a longer mean elimination half‑life. These findings suggest that dose adjustment of propranolol injection may be required for elderly patients (see CLINICAL PHARMACOLOGY, Special Populations, Geriatric). In general, dose selection for an elderly patient should be cautious, usually starting at the low end of the dosing range, reflecting the greater frequency of the decreased hepatic, renal or cardiac function, and of concomitant disease or other drug therapy.

Hepatic Insufficiency

Propranolol is extensively metabolized by the liver. Compared to normal subjects, patients with chronic liver disease have decreased clearance of propranolol, increased volume of distribution, decreased protein-binding and considerable variation in half life. Consideration should be given to lowering the dose of intravenously administered propranolol in patients with hepatic insufficiency.

ADVERSE REACTIONS

In a series of 225 patients, there were 6 deaths (see CLINICAL STUDIES). Cardiovascular events (hypotension, congestive heart failure, bradycardia, and heart block) were the most common. The only other event reported by more than one patient was nausea.

Other adverse events for intravenous propranolol, reported during post-marketing surveillance include cardiac arrest, dyspnea, and cutaneous ulcers.

The following adverse events have been reported with use of formulations of sustained- or immediate-release oral propranolol and may be expected with intravenous propranolol.

Cardiovascular

Bradycardia; congestive heart failure; intensification of AV block; hypotension; paresthesia of hands; thrombocytopenic purpura; arterial insufficiency, usually of the Raynaud type.

Central Nervous System

Light-headedness; mental depression manifested by insomnia, lassitude, weakness, fatigue; reversible mental depression progressing to catatonia; visual disturbances; hallucinations; vivid dreams; an acute reversible syndrome characterized by disorientation for time and place, short-term memory loss, emotional lability, slightly clouded sensorium, and decreased performance on neuropsychometrics. For immediate‑release formulations, fatigue, lethargy, and vivid dreams appear dose-related.

Gastrointestinal

Nausea, vomiting, epigastric distress, abdominal cramping, diarrhea, constipation, mesenteric arterial thrombosis, ischemic colitis.

Allergic

Pharyngitis and agranulocytosis; erythematous rash, fever combined with aching and sore throat; laryngospasm, and respiratory distress.

Respiratory

Bronchospasm.

Hematologic

Agranulocytosis, nonthrombocytopenic purpura, thrombocytopenic purpura.

Autoimmune

In extremely rare instances, systemic lupus erythematosus has been reported.

Miscellaneous

Alopecia, LE-like reactions, psoriaform rashes, dry eyes, male impotence, and Peyronie’s disease have been reported rarely. Oculomucocutaneous reactions involving the skin, serous membranes and conjunctivae reported for a beta-blocker (practolol) have not been associated with propranolol.

To report SUSPECTED ADVERSE REACTIONS, contact Hikma Pharmaceuticals USA Inc. at 1-877-845-0689 or FDA at 1-800-FDA-1088 or www.fda.gov/medwatch.

OVERDOSAGE

Propranolol is not significantly dialyzable. In the event of overdose or exaggerated response, the following measures should be employed:

Hypotension and bradycardia have been reported following propranolol overdose and should be treated appropriately. Glucagon can exert potent inotropic and chronotropic effects and may be particularly useful for the treatment of hypotension or depressed myocardial function after a propranolol overdose. Glucagon should be administered as 50-150 mcg/kg intravenously followed by continuous drip of 1-5 mg/hour for positive chronotropic effect. Isoproterenol, dopamine, or phosphodiesterase inhibitors may also be useful. Epinephrine, however, may provoke uncontrolled hypertension. Bradycardia can be treated with atropine or isoproterenol. Serious bradycardia may require temporary cardiac pacing.

The electrocardiogram, pulse, blood pressure, neurobehavioral status and intake and output balance must be monitored. Isoproterenol and aminophylline may be useful for bronchospasm.

DOSAGE AND ADMINISTRATION

Parenteral drug products should be inspected visually for particulate matter and discoloration prior to administration, whenever solution and container permit.

The usual dose is 1 to 3 mg administered under careful monitoring, such as electrocardiography and central venous pressure. The rate of administration should not exceed 1 mg (1 mL) per minute to diminish the possibility of lowering blood pressure and causing cardiac standstill. Sufficient time should be allowed for the drug to reach the site of action even when a slow circulation is present. If necessary, a second dose may be given after two minutes. Thereafter, additional drug should not be given in less than four hours. Additional propranolol hydrochloride should not be given when the desired alteration in rate or rhythm is achieved.

Transfer to oral therapy as soon as possible.

HOW SUPPLIED

Each mL contains 1 mg of Propranolol Hydrochloride, USP in Water for Injection, USP. The pH is adjusted with anhydrous Citric Acid, USP. Supplied as: 1 mL vials in boxes of 10 (NDC 0143-9872-10).

Store at 20° to 25°C (68° to 77°F) [See USP Controlled Room Temperature]. Protect from freezing or excessive heat.

Manufactured by: HIKMA FARMACÊUTICA (PORTUGAL), S.A.
Estrada do Rio da Mó, 8, 8A e 8B – Fervença – 2705-906 Terrugem SNT, PORTUGAL

Distributed by:

Hikma Pharmaceuticals USA Inc.
Berkeley Heights, NJ 07922

Revised: May 2022
PIN166-WES/7

PRINCIPAL DISPLAY PANEL

NDC 0143-9872-01 Rx only
Propranolol
Hydrochloride Injection, USP
1 mg/mL
For IV use ONLY
1 mL Single Dose Vial

NDC 0143-9872-10 Rx only
Propranolol
Hydrochloride Injection, USP
1 mg/mL
For Intravenous use ONLY
10 x 1 mL Single Dose Vials